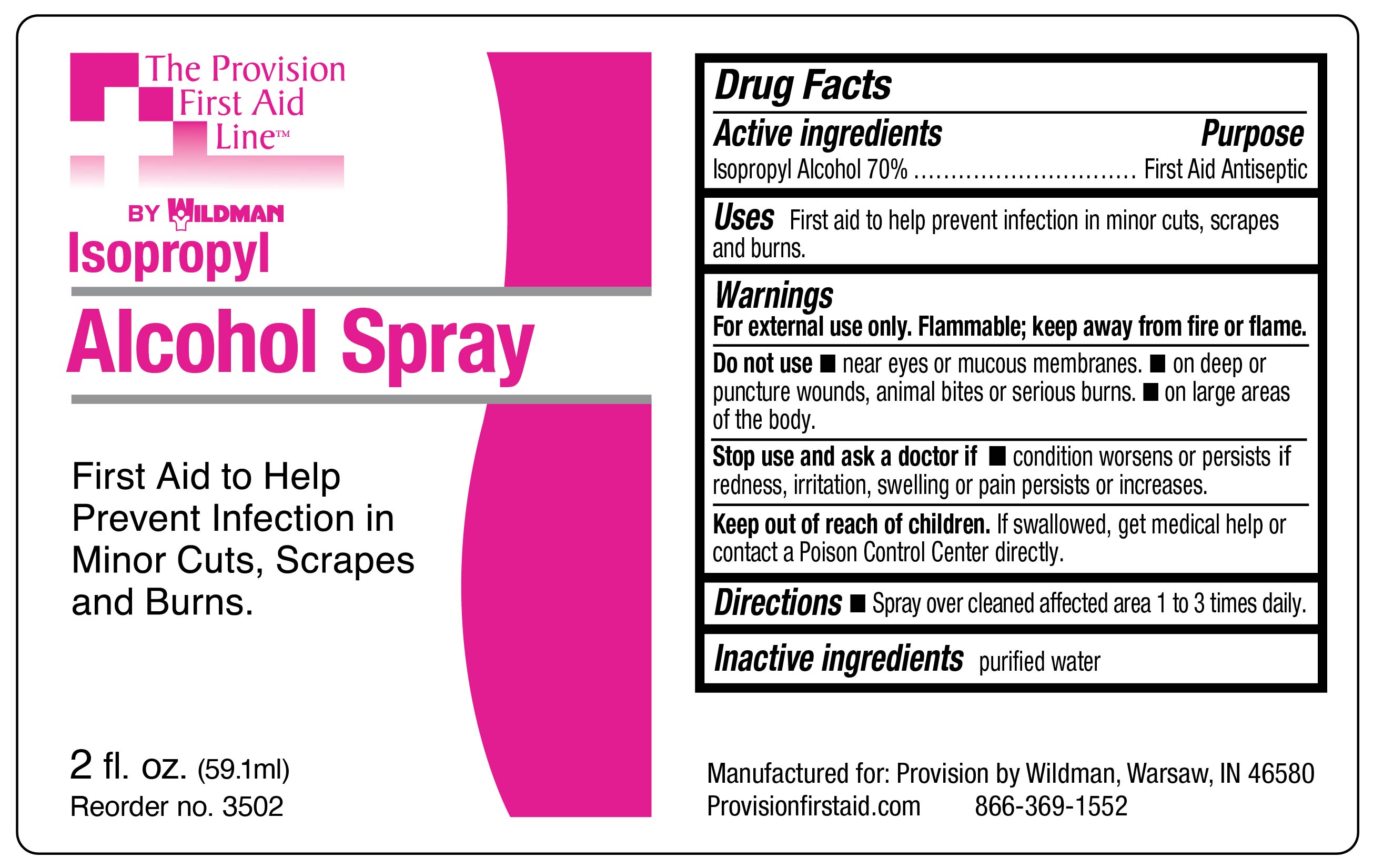 DRUG LABEL: Isopropyl Alcohol
NDC: 84269-3502 | Form: SPRAY
Manufacturer: Wildman Business Group
Category: otc | Type: HUMAN OTC DRUG LABEL
Date: 20240901

ACTIVE INGREDIENTS: ISOPROPYL ALCOHOL 700 mL/1 L
INACTIVE INGREDIENTS: WATER

69103-5500, Isopropyl alcohol spray

Active Ingredients

Isopropyl Alcohol 70%

Purpose

First Aid Antiseptic

Uses

First aid to help prevent infection in minor cuts, scrapes and burns

Warnings

For external use only.

Flammable keep away from fire or flame.

Do not use

- near eyes or mucous membranes
- on deep or puncture wounds, animal bites or serious burns

Keep out of reach of children

Caution

- not for use on large areas of the body
- if redness, irritation, swelling or pain persists or increases, discontinue use and consult a physician.

Directions

- spray over cleaned affected area 1 to 3 times daily

Inactive Ingredients

purified water

Principal Display Panel – 2 fl. oz Bottle Label, IPA Spray

Provision by Wildman

Isopropyl
Alcohol Spray

First Aid to Help
Prevent Infection in
Minor Cuts, Scrapes
and Burns.

2 fl. oz. (59.1 ml)

Reorder no. 3502